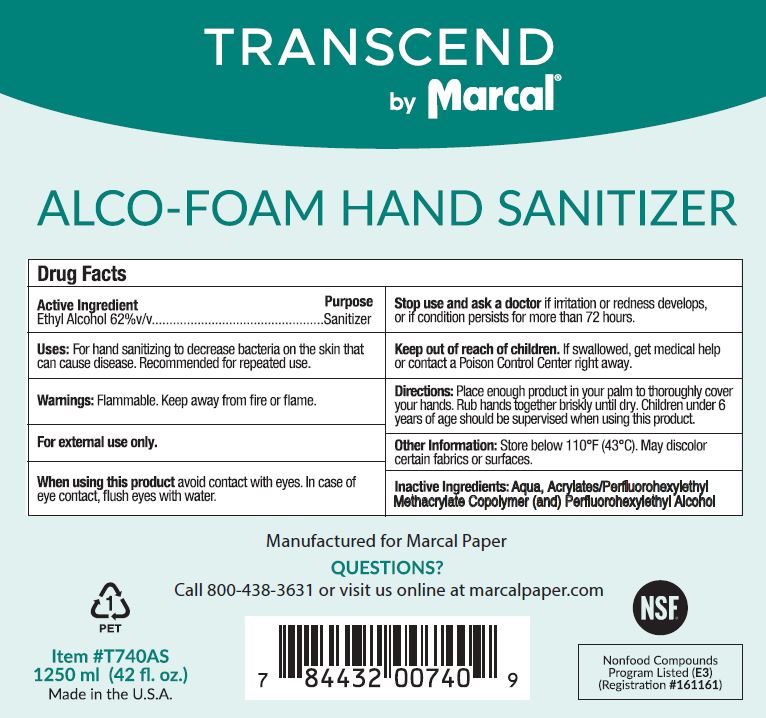 DRUG LABEL: Transcend Alco-Foam Hand Sanitizer
NDC: 81792-001 | Form: LIQUID
Manufacturer: Von Drehle Corporation
Category: otc | Type: HUMAN OTC DRUG LABEL
Date: 20240308

ACTIVE INGREDIENTS: ALCOHOL 62 mL/100 mL
INACTIVE INGREDIENTS: 2-(PERFLUOROHEXYL)ETHANOL; BUTYL ACRYLATE/METHYL METHACRYLATE/PERFLUOROHEXYLETHYL METHACRYLATE COPOLYMER (SALUS AF)

Active Ingredient

Ethyl Alcohol 62%v/v

Purpose

Sanitizer

Uses:

For hand sanitizing to decrease bacteria on the skin that can cause disease. Recommended for repeated use.

Warnings:

Flammable. Keep away from fire or flame

For external use only.

When using this product avoid contact with eyes. In case of eye contact, flush eyes with water.

Stop use and ask a doctor if irritationor redness develops, or if condition persists for more than 72 hours.

Keep out of reach of children. If swallowed, get medical help or contact a Poison Control Center right away.

Directions:

Place enough product in your palm to thoroughly cover your hands. Rub hands together briskly until dry.Children under 6 years of age should be supervised when using this product.

Other Information:

Store below 110°F (43°C). May discolor certain fabrics or surfaces.

Inactive Ingredients:

Aqua, Acrylates/Perfluorohexylethyl Methacrylate Copolymer (and) Perfluorohexylethyl Alcohol

PACKAGE LABEL

TRANSCEND

by Marcal

ALCO-FOAM HAND SANITIZER

Manufactured for Marcal Paper

QUESTIONS

Call 800-438-3631 or visit us online at marcalpaper.com

1

PET

Item #T740AS

1250 ml (42 fl. oz.)

Made in the U.S.A.

NSF

Nonfood Compounds

Program Listed (E3)

(Registration #161161)